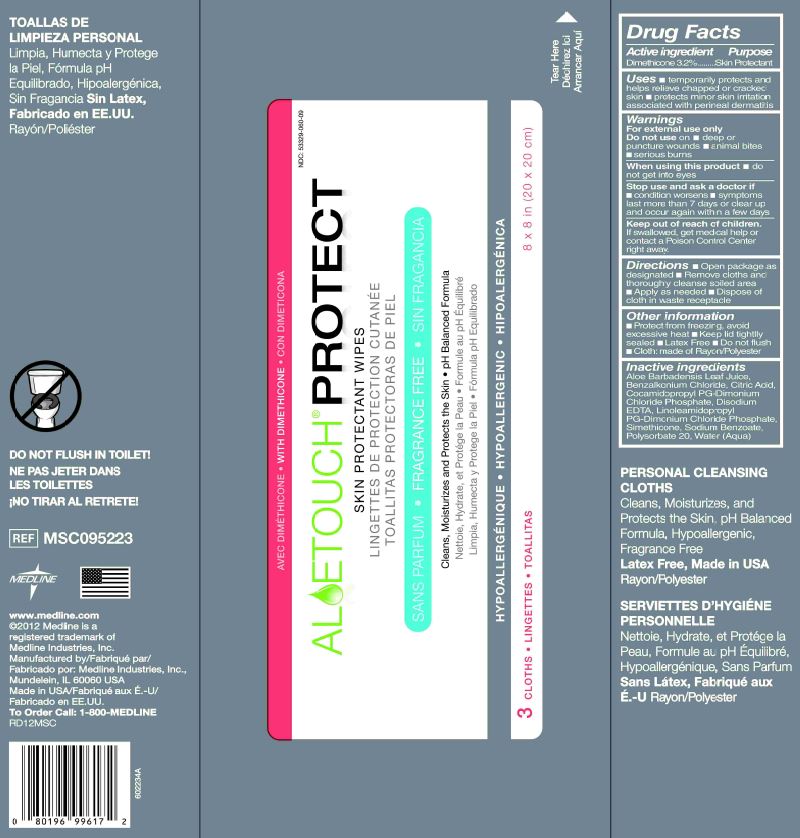 DRUG LABEL: Readybath TPC
NDC: 53329-060 | Form: CLOTH
Manufacturer: Medline Industries, Inc.
Category: otc | Type: HUMAN OTC DRUG LABEL
Date: 20260130

ACTIVE INGREDIENTS: DIMETHICONE 0.544 g/1 1
INACTIVE INGREDIENTS: WATER; POLYSORBATE 20; SODIUM BENZOATE; BENZALKONIUM CHLORIDE; ALOE VERA LEAF; CITRIC ACID MONOHYDRATE

060 Aloetouch Protect

Active ingredient

Dimethicone 3.2%

Purpose

Skin Protectant

Uses

- temporarily protects and helps relieve chapped or cracked skin
- protects minor skin irritation associated with perineal dermatitis

Warnings

For external use only

Do not use on

- deep or puncture wounds
- animal bites
- serious burns

When using this product

- avoid direct contact with eyes

Stop use and ask a doctor if

- condition worsens
- symptoms last more than 7 days or clear up and occur again within a few days

Keep out of reach of children.

If swallowed, get medical help or consult a Poison Control Center right away.

Directions

- Open package as designated
- Remove cloths and thoroughly cleanse soiled area
- Apply as needed
- Dispose of cloth in waste receptacle

Other information

- Protect from freezing, avoid excessive heat
- Keep lid tightly sealed
- Not made with Natural Rubber Latex
- Do not flush
- Cloth: made of Rayon/Polyester

Inactive ingredients

Aloe Barbadensis Leaf Juice, Benzalkonium Chloride, Citric Acid, Cocamidopropyl PG-Dimonium Chloride Phosphate, Disodium EDTA, Linoleamidopropyl PG-Dimonium Chloride Phosphate, Simethicone, Sodium Benzoate, Polysorbate 20, Water (Aqua)